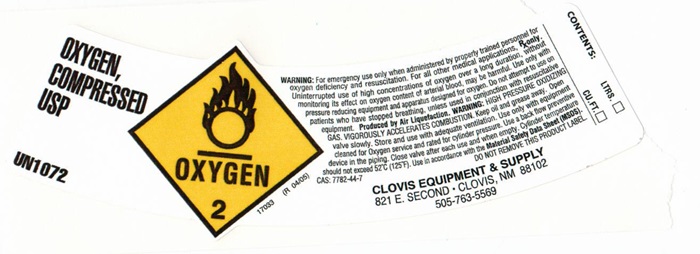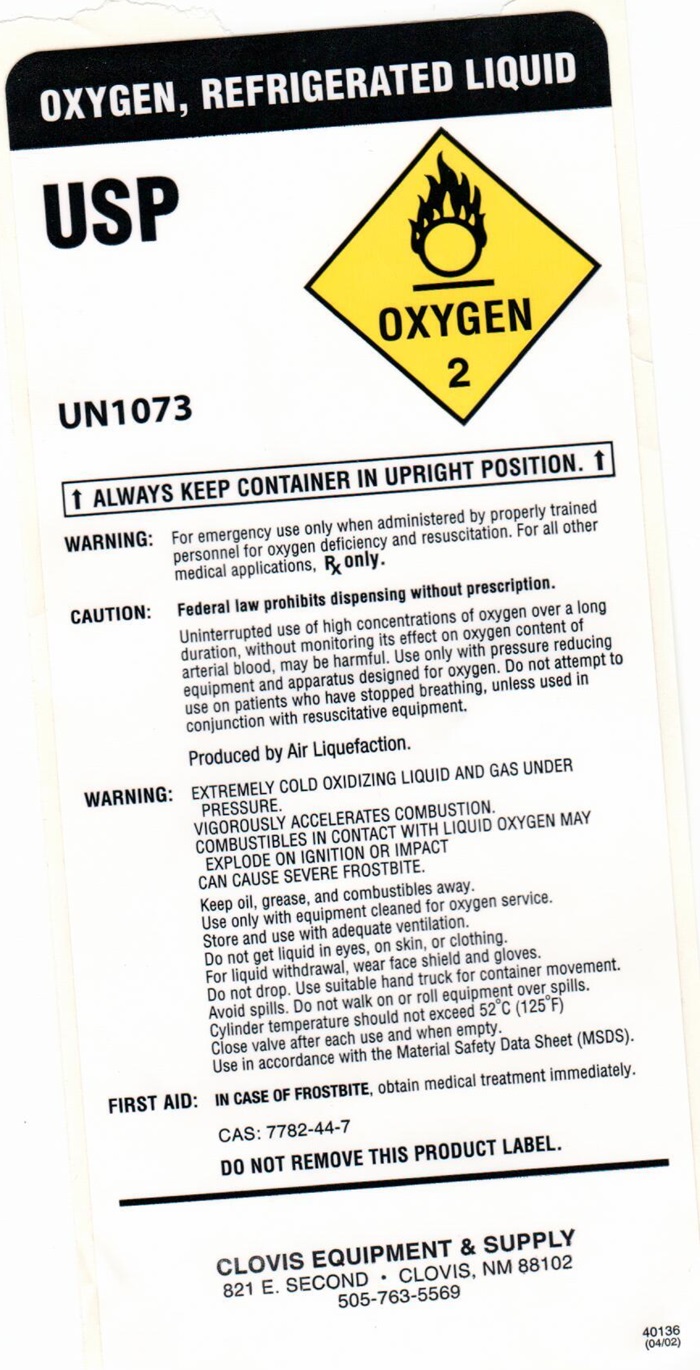 DRUG LABEL: OXYGEN
NDC: 53730-001 | Form: GAS
Manufacturer: Clovis Equipment & Supply Company
Category: prescription | Type: HUMAN PRESCRIPTION DRUG LABEL
Date: 20251023

ACTIVE INGREDIENTS: OXYGEN 99 L/100 L

OXYGEN

OXYGEN COMPRESSED USP product label

OXYGEN COMPRESSED USP
UN1072
OXYGEN 2

17033 (R 04/05)

WARNING:For emergency use only when administered by properly trained personnel for oxygen deficiency and resuscitation. For all other medical applications Rx only. Uninterrupted use of high concentrations of oxygen over a long duration, without monitoring its effect on oxygen content of arterial blood, may be harmful. Use only with pressure reducing equipment and apparatus designed for oxygen. Do not attempt to use on patients who have stopped breathing, unless used in conjunction with resuscitative equipment. Produced by Air Liquefaction.HIGH PRESSURE OXIDIZING GAS, VIGOROUSLY ACCELERATES COMBUSTION. Keep oil and grease away. Open valve slowly. Store and use with adequate ventitation. Use only with equipment cleaned for Oxygen service and rated for cylinder pressure. Use a back flow preventive device in the piping. Close valve after each use and when empty. Cylinder pressure should not exceed 52°C (125°F). Use in accordance with the Material Safety Data Sheet (MSDS)

CAS: 7782-44-7 DO NOT REMOVE THIS PRODUCT LABEL

CLOVIS EQUIPMENT & SUPPLY

821 E. SECOND • CLOVIS, NM 88102

505-763-5569

OXYGEN, REFIGERATED LIQUID USP

OXYGEN, REFIGERATED LIQUID
USP
OXYGEN 2

UN1073

↑ ALWAYS KEEP CONTAINER IN UPRIGHT POSITION. ↑

WARNING:For emergency use only when administered by properly trained personnel for oxygen deficiency and resuscitation. For all other medical applications, Rx only.

CAUTION:Federal law prohibits dispensing without prescription.

Uninterrupted use of high concentrations of oxygen over a long duration, without monitoring its effect on oxygen content of arterial blood, may be harmful. Use only with pressure reducing equipment and apparatus designed for oxygen. Do not attempt to use on patients who have stopped breathing, unless used in conjunction with resuscitative equipment.

Produced by Air Liquefaction

WARNING:EXTREMELY COLD OXIDIZING LIQUID AND GAS UNDER PRESSURE.

VIGOROUSLY ACCELERATES COMBUSTION.

COMBUTIBLES IN CONTACT WITH LIQUID OXYGEN MAY EXPLODE ON IGNITION OR IMPACT.

CAN CAUSE SEVERE FROSTBITE.

Keep oil, grease, and combustibles away.

Use only with equipment cleaned for oxygen service.

Store and use with adequate ventilation.

Do not get liquid in eyes, on skin, or clothing.

For liquid withdraw, wear face shield and gloves.

Do not drop. Use suitable hand truck for container movement.

Avoid spills. Do not walk on or roll equipment over spills.

Cylinder pressure should not exceed 52°C (125°F).

Close valve after each use and when empty.

Use in accordance with the Material Safety Data Sheet (MSDS)

First Aid: IN CASE OF FROSTBITE,obtain medical treatment immediately.

CAS: 7782-44-7

DO NOT REMOVE THIS PRODUCT LABEL.

CLOVIS EQUIPMENT & SUPPLY

821 E. SECOND • CLOVIS, NM 88102

505-763-5569

40136

(04/02)